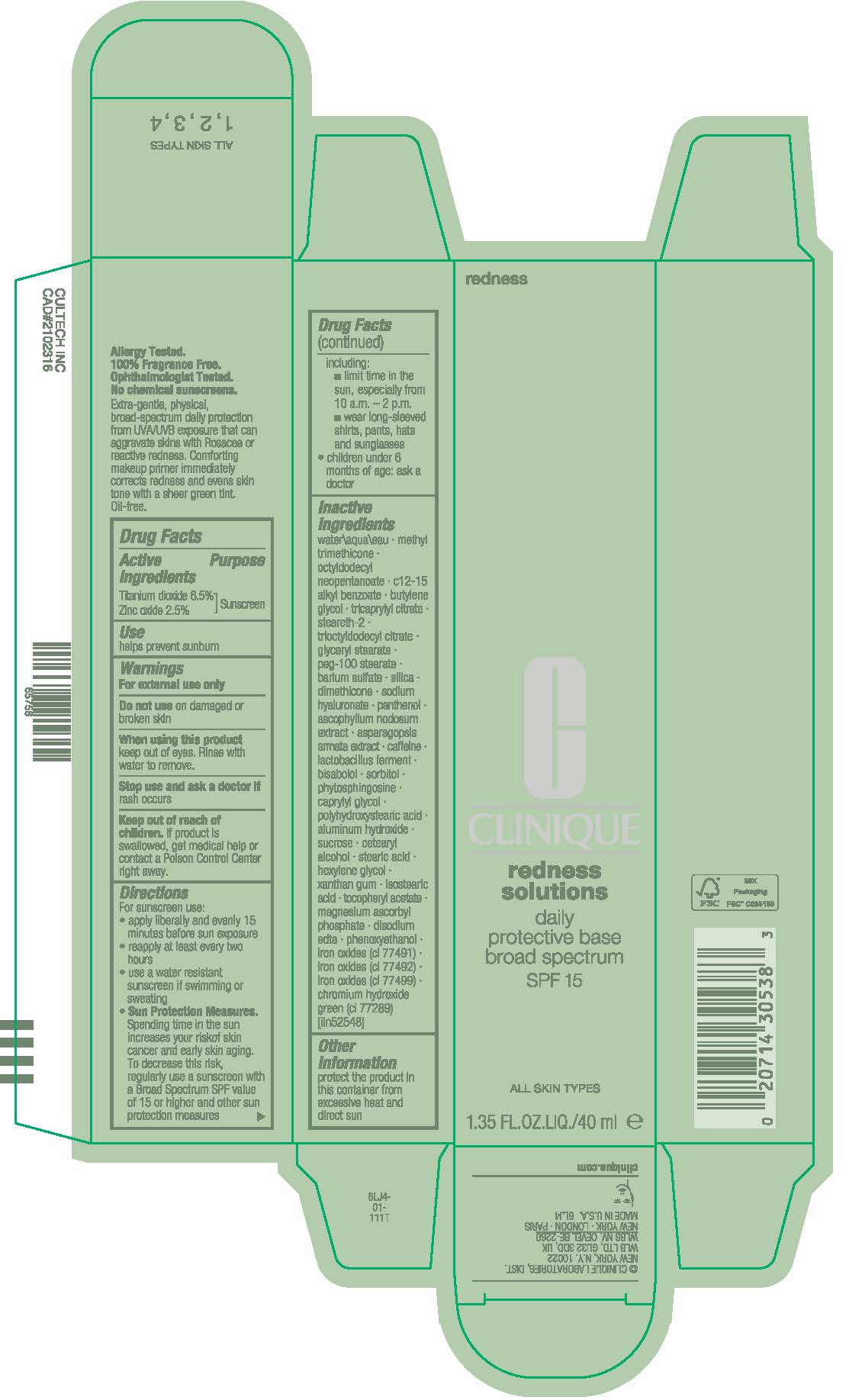 DRUG LABEL: REDNESS solutions DAILY PROTECTIVE BASE BROAD SPECTRUM SPF 15
NDC: 49527-019 | Form: CREAM
Manufacturer: CLINIQUE LABORATORIES LLC
Category: otc | Type: HUMAN OTC DRUG LABEL
Date: 20250225

ACTIVE INGREDIENTS: TITANIUM DIOXIDE 65 mg/1 mL; ZINC OXIDE 25 mg/1 mL
INACTIVE INGREDIENTS: ASCOPHYLLUM NODOSUM; POLYHYDROXYSTEARIC ACID (2300 MW); LIMOSILACTOBACILLUS REUTERI; HYALURONATE SODIUM; SORBITOL; PHYTOSPHINGOSINE; CAPRYLYL GLYCOL; ALUMINUM HYDROXIDE; STEARIC ACID; HEXYLENE GLYCOL; XANTHAN GUM; EDETATE DISODIUM ANHYDROUS; PHENOXYETHANOL; FERRIC OXIDE RED; FERRIC OXIDE YELLOW; FERROSOFERRIC OXIDE; CHROMIUM HYDROXIDE GREEN; WATER; METHYL TRIMETHICONE; OCTYLDODECYL NEOPENTANOATE; ALKYL (C12-15) BENZOATE; BUTYLENE GLYCOL; TRICAPRYLYL CITRATE; GLYCERYL MONOSTEARATE; PEG-100 STEARATE; BARIUM SULFATE; SILICON DIOXIDE; SUCROSE; CAFFEINE; DIMETHICONE; CETOSTEARYL ALCOHOL; ISOSTEARIC ACID; LEVOMENOL; MAGNESIUM ASCORBYL PHOSPHATE; STEARETH-2; TRIOCTYLDODECYL CITRATE; ASPARAGOPSIS ARMATA; ALPHA-TOCOPHEROL ACETATE; LIMOSILACTOBACILLUS FERMENTUM; PANTHENOL

REDNESS SOLUTIONS DAILY PROTECTIVE BASE BROAD SPECTRUM SPF 15

Drug Facts

Active ingredients

Titanium dioxide 6.5%

Zinc oxide 2.5%

Purpose

Sunscreen

Use

helps prevent sunburn

Warnings

For external use only

Do not use on damaged or broken skin

When using this product keep out of eyes. Rinse with water to remove.

Stop use and ask a doctor if rash occurs

Keep out of reach of children. If product is swallowed, get medical help or contact a Poison Control Center right away.

Directions

For sunscreen use:

- apply liberally 15 minutes before sun exposure
- reapply at least every two hours
- use a water resistant sunscreen if swimming or sweating
- Sun Protection Measures. Spending time in the sun increases your risk of skin cancer and early skin aging. To decrease this risk, regularly use a sunscreen with a Broad Spectrum SPF value of 15 or higher and other sun protection measures including:
  - limit time in the sun, especially from 10 a.m. – 2 p.m.
  - wear long-sleeved shirts, pants, hats and sunglasses
- children under 6 months of age: ask a doctor

Inactive ingredients

water\aqua\eau,methyl trimethicone,octyldodecyl neopentanoate,c12-15 alkyl benzoate,butylene glycol,tricaprylyl citrate,steareth-2,trioctyldodecyl citrate,glyceryl stearate,peg-100 stearate,barium sulfate,silica,dimethicone,sodium hyaluronate,panthenol,ascophyllum nodosum extract,asparagopsis armata extract,caffeine,lactobacillus ferment,bisabolol,sorbitol,phytosphingosine,caprylyl glycol,polyhydroxystearic acid,aluminum hydroxide,sucrose,cetearyl alcohol,stearic acid,hexylene glycol,xanthan gum,isostearic acid,tocopheryl acetate,magnesium ascorbyl phosphate,disodium edta,phenoxyethanol,iron oxides (ci 77491),iron oxides (ci 77492),iron oxides (ci 77499),chromium hydroxide green (ci 77289) <iln52548>

Other information

protect the product in this container from excessive heat and direct sun

PRINCIPAL DISPLAY PANEL - 40 ml Bottle Carton

redness

CLINIQUE

redness
solutions

daily
protective base
broad spectrum
SPF 15

ALL SKIN TYPES

1.35 FL.OZ.LIQ./40 ml e